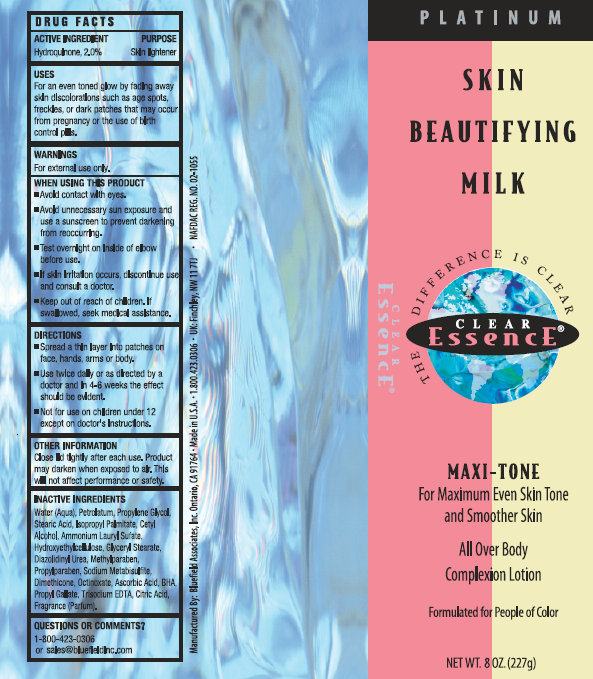 DRUG LABEL: Skin Beautifying Milk
NDC: 16708-001 | Form: CREAM
Manufacturer: Bluefield Associates, Inc.
Category: otc | Type: HUMAN OTC DRUG LABEL
Date: 20151028

ACTIVE INGREDIENTS: HYDROQUINONE 0.02 g/1 g
INACTIVE INGREDIENTS: ASCORBIC ACID; PROPYL GALLATE; WATER; EDETATE TRISODIUM; GLYCERYL MONOSTEARATE; CETYL ALCOHOL; ISOPROPYL PALMITATE; STEARIC ACID; AMMONIUM LAURYL SULFATE; DIMETHICONE; SODIUM METABISULFITE; BUTYLATED HYDROXYTOLUENE; METHYLPARABEN; PROPYLPARABEN; DIAZOLIDINYL UREA; PETROLATUM

Skin Beautifying Milk

Active Ingredient

Hydroquinone 2.0%

Purpose

Skin Lightener

Uses:

- For an even toned glow by fading away skin discolorations such as age spots, freckles, or dark patches that may occur from pregnancy or the use of birth control pills.

Warnings

For External use only.

WHEN USING THIS PRODUCT

- Avoid contact with eyes.
- Avoid unnecessary sun exposure and use a sunscreen to prevent darkening from reoccuring.
- Test overnight on Inside of elbow before use.
- If skin irritation occurs, discontinue use and consult a doctor.

Do Not use on

children under 12 years of age unless directed by a doctor.

Keep out of the reach of children.

If swallowed, seek medical assistance.

Questions or Comments?

1-800-423-0306 or sales@bluefieldInc.com

Directions

- Spread a thin layer into patches on face, hands, arms or body..
- Use twice daily or as directed by a doctor and in 4-6 weeks the effect should be evident.
- Not for use on children under 12 except on doctor's intructions.

OTHER INFORMATION

Close lid tightly after each use. Product may darken when exposed to air. This will not affect performance or safety.

Inactive Ingredients

Water (Aqua), White Petrolatum, Cetyl Alcohol, Isopropyl Palmitate, Stearic Acid, Propylene Glycol, Stearic Acid, Ammonium Lauryl Sulfate, Dimethicone, Diazolidinyl Urea, Methylparaben, Propylparaben, Glyceryl Stearate,Sodium Metabisulfite, Ascorbic Acid, BHA, Propul Gallate,Trisodium EDTA, Fragrance (Parfum).